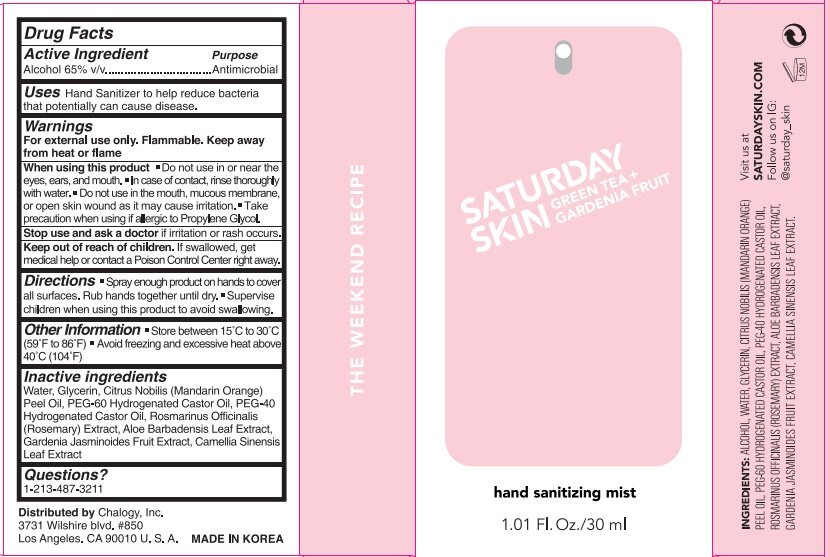 DRUG LABEL: Saturday Skin Hand Sanitizing Mist
NDC: 80746-100 | Form: SPRAY
Manufacturer: CHALOGY, INC.
Category: otc | Type: HUMAN OTC DRUG LABEL
Date: 20201116

ACTIVE INGREDIENTS: ALCOHOL 65 mL/65 mL
INACTIVE INGREDIENTS: MANDARIN OIL; ROSEMARY; GLYCERIN; PEG-60 HYDROGENATED CASTOR OIL; GARDENIA JASMINOIDES FRUIT; GREEN TEA LEAF; ALOE VERA LEAF; POLYOXYL 40 HYDROGENATED CASTOR OIL; WATER

ACTIVE INGREDIENT

Alcohol 65% v/v - purpose: Antimicrobial

Purpose: Antimicrobial

INDICATIONS AND USAGE

Hand Sanitizer to help reduce bacteria that potentially can cause disease

WARNINGS

For external use only. Flammable. Keep away from fire or flame

Do not use in or near the eyes, ears, and mouth. In case of contact, rinse thoroughly with water. Do not use in the mouth, mucous membrane, or open skin wound as it may cause irritation. Take precaution when using if allergic to Propylene Glycol.

STOP USE

and ask a doctor if irritation or rash occurs.

KEEP OUT OF REACH OF CHILDREN

If swallowed, get medical help or contact a Poison Control Center right away.

DOSAGE AND ADMINISTRATION

Spray once in the hand

OTHER SAFETY INFORMATION

Store between 15˚C to 30˚C (59˚F to 86˚F), Avoid freezing and excessive heat above 40˚C (104˚F)

INACTIVE INGREDIENT

Water, Glycerin, Citrus Nobilis (Mandarin Orange) Peel Oil, PEG-60 Hydrogenated Castor Oil, PEG-40 Hydrogenated Castor Oil, Rosmarinus Officinalis (Rosemary) Extract, Aloe Barbadensis Leaf Extract, Gardenia Jasminoides Fruit Extract, Camellia Sinensis Leaf Extract

QUESTIONS

213-487-3211

PACKAGE LABEL

30 mL NDC 80746-100-01